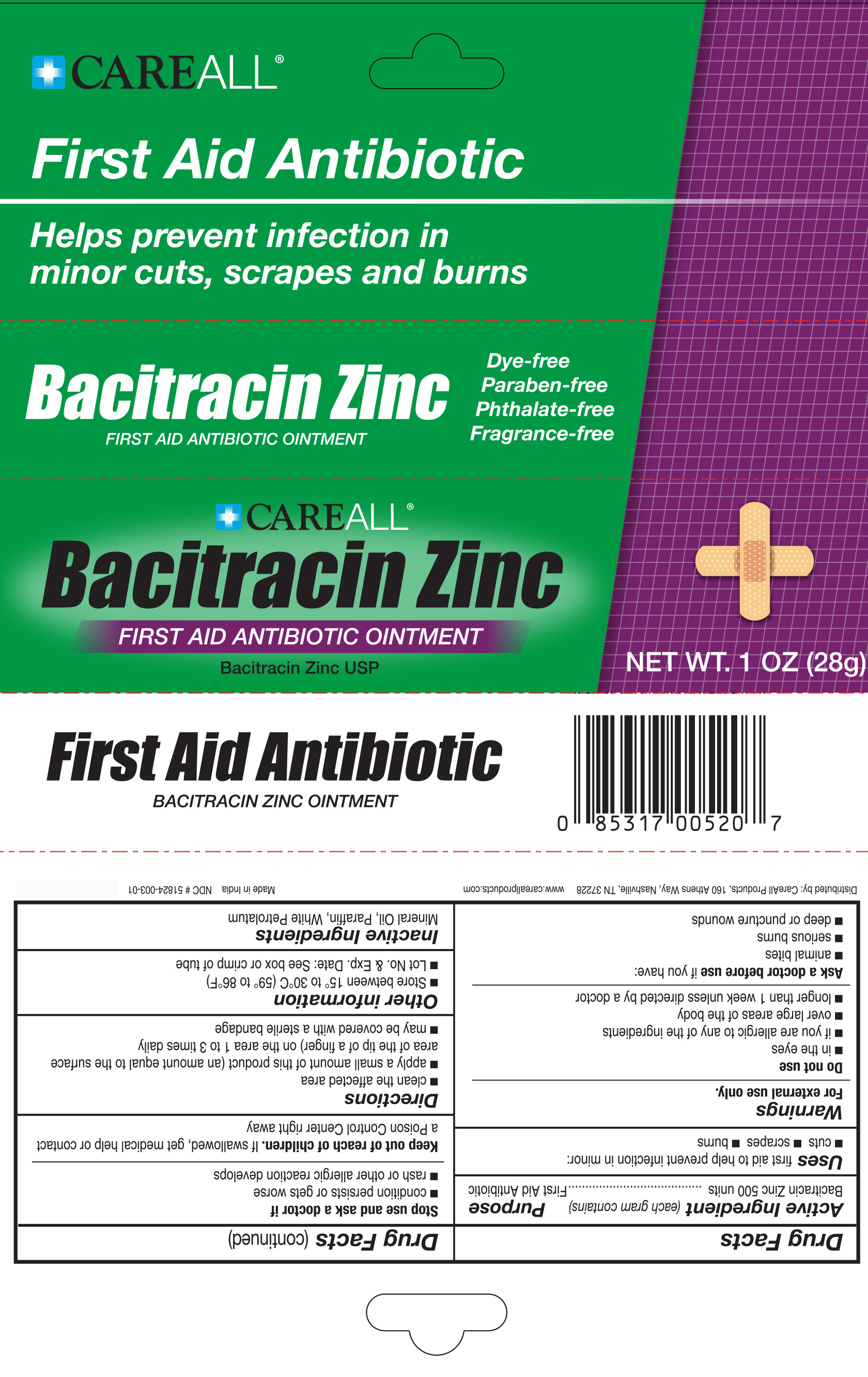 DRUG LABEL: CAREALL Bacitracin
NDC: 51824-003 | Form: CREAM
Manufacturer: New World Imports, Inc
Category: otc | Type: HUMAN OTC DRUG LABEL
Date: 20251202

ACTIVE INGREDIENTS: BACITRACIN ZINC 500 [USP'U]/1 g
INACTIVE INGREDIENTS: PARAFFIN; MINERAL OIL; WHITE PETROLATUM

Drug Facts

ACTIVE INGREDIENT

Bacitracin Zinc

PURPOSE

First Aid Antibiotic

Keep out of Reach of Children. If swallowed, get medical help or contact a Poison Control Center immediately.

INDICATIONS AND USAGE

First aid to help prevent infection in minor:

- cuts
- scrapes
- burns

WARNINGS

For external use only

Do not use:

- in the eyes
- if you are allergic to any of the ingredients
- over large areas of the body
- longer than 1 week unless directed by a doctor

Ask a doctor before use if you have:

- animal bites
- serious burns
- deep or puncture wounds

Stop use and ask a doctor if

- condition persists or gets worse
- rash or other allergic reaction develops

DOSAGE AND ADMINISTRATION

- clean the affected area
- apply a small amount of this product (an amount equal to the surface area of the tip of the finger) on the area 1 to 3 times daily
- may be covered with a sterile bandage

INACTIVE INGREDIENT

Mineral Oil, Paraffin, White Petrolatum